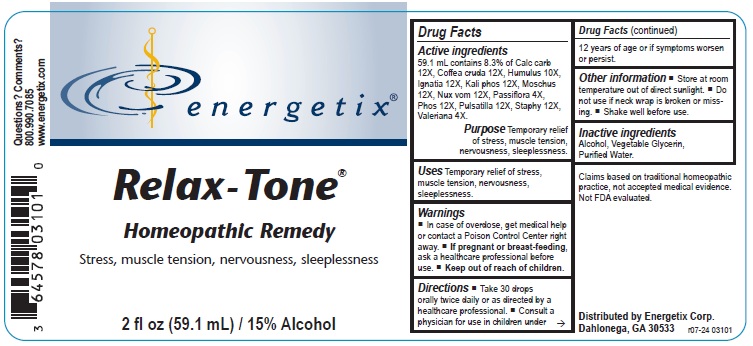 DRUG LABEL: Relax-Tone
NDC: 64578-0091 | Form: LIQUID
Manufacturer: Energetix Corporation
Category: homeopathic | Type: HUMAN OTC DRUG LABEL
Date: 20250711

ACTIVE INGREDIENTS: OYSTER SHELL CALCIUM CARBONATE, CRUDE 12 [hp_X]/1 mL; ARABICA COFFEE BEAN 12 [hp_X]/1 mL; HOPS 10 [hp_X]/1 mL; STRYCHNOS IGNATII SEED 12 [hp_X]/1 mL; POTASSIUM PHOSPHATE, DIBASIC 12 [hp_X]/1 mL; MOSCHUS MOSCHIFERUS MUSK SAC RESIN 12 [hp_X]/1 mL; STRYCHNOS NUX-VOMICA SEED 12 [hp_X]/1 mL; PASSIFLORA INCARNATA FLOWERING TOP 4 [hp_X]/1 mL; PHOSPHORUS 12 [hp_X]/1 mL; PULSATILLA VULGARIS 12 [hp_X]/1 mL; DELPHINIUM STAPHISAGRIA SEED 12 [hp_X]/1 mL; VALERIAN 4 [hp_X]/1 mL
INACTIVE INGREDIENTS: WATER; GLYCERIN; ALCOHOL

Relax-Tone

ACTIVE INGREDIENT

Active ingredients 59.1 mL contains 8.3% of Calc carb 12X, Coffea cruda 12X, Humulus 10X, Ignatia 12X, Kali phos 12X, Moschus 12X, Nux vom 12X, Passiflora 4X, Phos 12X, Pulsatilla 12X, Staphy 12X, Valeriana 4X.

Claims based on traditional homeopathic practice, not accepted medical evidence. Not FDA evaluated.

Uses

Temporary relief of stress, muscle tension, nervousness, sleeplessness.

Warnings

- In case of overdose, get medical help or contact a Poison Control Center right away.
- If pregnant or breast-feeding, ask a healthcare professional before use.

- Keep out of reach of children.

Directions

- Take 30 drops orally twice daily or as directed by a healthcare professional.
- Consult a physician for use in children under 12 years of age or if symptoms worsen or persist.

Other information

- Store at room temperature out of direct sunlight.
- Do not use if neck wrap is broken or missing.
- Shake well before use.

Inactive ingredients

Alcohol, Vegetable Glycerin, Purified Water.

QUESTIONS

Distributed by Energetix Corp.

Dahlonega, GA 30533

Questions? 800.990.7085

www.energetix.com

PACKAGE LABEL

energetix®

Relax-Tone

Homeopathic Remedy

Stress, muscle tension, nervousness, sleeplessness

2 fl oz (59.1 mL) / 15% Alcohol

PURPOSE

Purpose Temporary relief of stress, muscle tension, nervousness, sleeplessness.